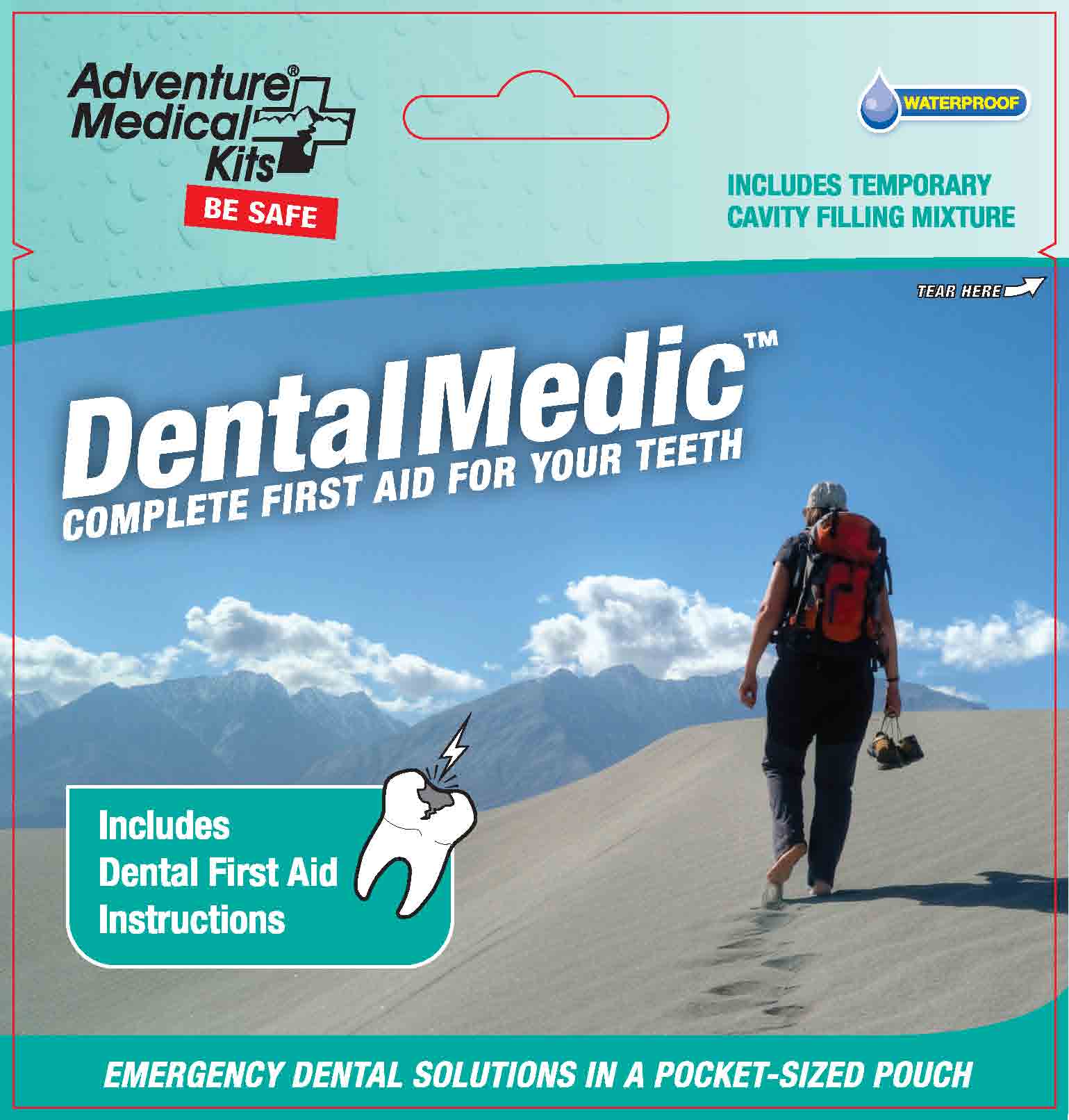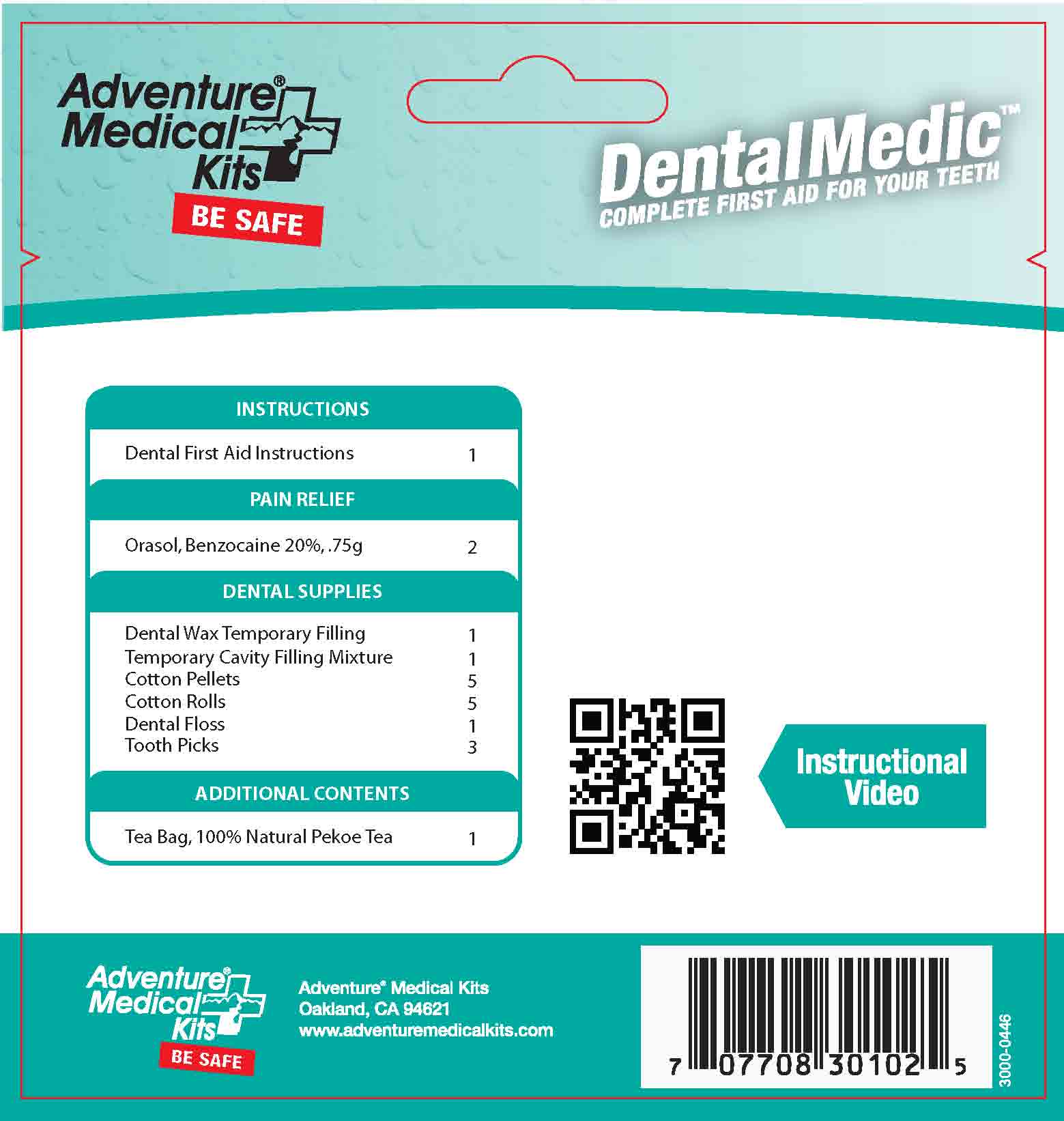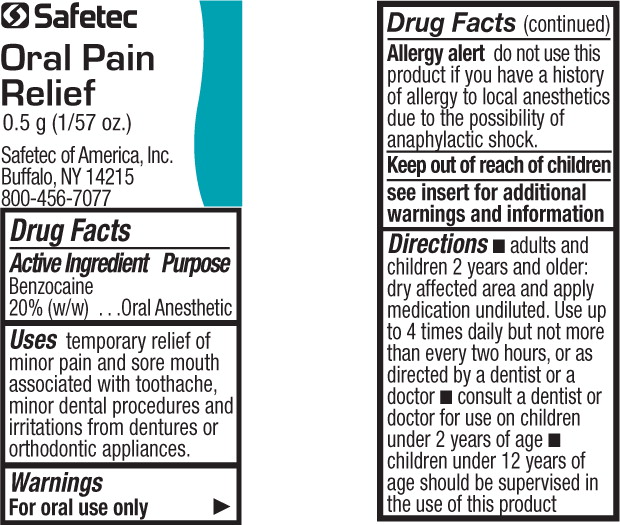 DRUG LABEL: Adventure Medical Kits Dental Medic
NDC: 44224-0102 | Form: KIT | Route: TOPICAL
Manufacturer: Tender Corporation
Category: otc | Type: HUMAN OTC DRUG LABEL
Date: 20170316

ACTIVE INGREDIENTS: BENZOCAINE 200 mg/1 g
INACTIVE INGREDIENTS: PEPPERMINT OIL; POLYETHYLENE GLYCOL 400; POLYETHYLENE GLYCOL 3350; SACCHARIN SODIUM; SORBIC ACID

Adventure Medical Kits Dental Medic

Active Ingredient - Oral Pain Relief

Benzocaine 20%

Purpose - Oral Pain Relief

Oral Pain Reliever

Uses - Oral Pain Reliever

Temporarily relieves pain caused by: toothache, dental work, minor irritation or injury of the mouth and gums, canker sores, cheek bites, gum sores, and denture irritation.

Warnings - Oral Pain Relief

For oral use only. Avoid contact with eyes.

Allergy alert

Do not use this product if you have a history of allergy to local anesthetics, such as procaine, butacaine, benzocaine, or other “caine” anesthetics due to the possibility of anaphylactic shock.

When using this product

Do not use for more than 7 days unless directed by a dentist or doctor. If sore mouth symptoms do not improve in 7 days; if irritation, pain or redness persists or worsens; or if swelling, rash, fever or other allergic reaction develops, see your doctor or dentist promptly. Do not exceed recommended dosage.

Keep out of reach of children

If more than used for pain relief is accidentally swallowed, get medical help or contact a Poison Control Center right away.

Directions - Oral Pain Relief

Adults and children 2 years and older: dry affected area and apply medication undiluted. Use up to 4 times daily, but not more than every two hours, or as directed by a dentist or doctor.

Consult a dentist or doctor for use on children under 2 years of age

Children under 12 years of age should be supervised in the use of this product

Other Information - Oral Pain Relief

Do not use if packet is torn, cut, or opened

Store at room temperature, 15º to 30ºC (59º to 86ºF)

Avoid contact with eyes

Inactive Ingredients - Oral Pain Relief

PEG 400, PEG 3350, peppermint oil, sodium saccharin, sorbic acid

Keep out of Reach of Children